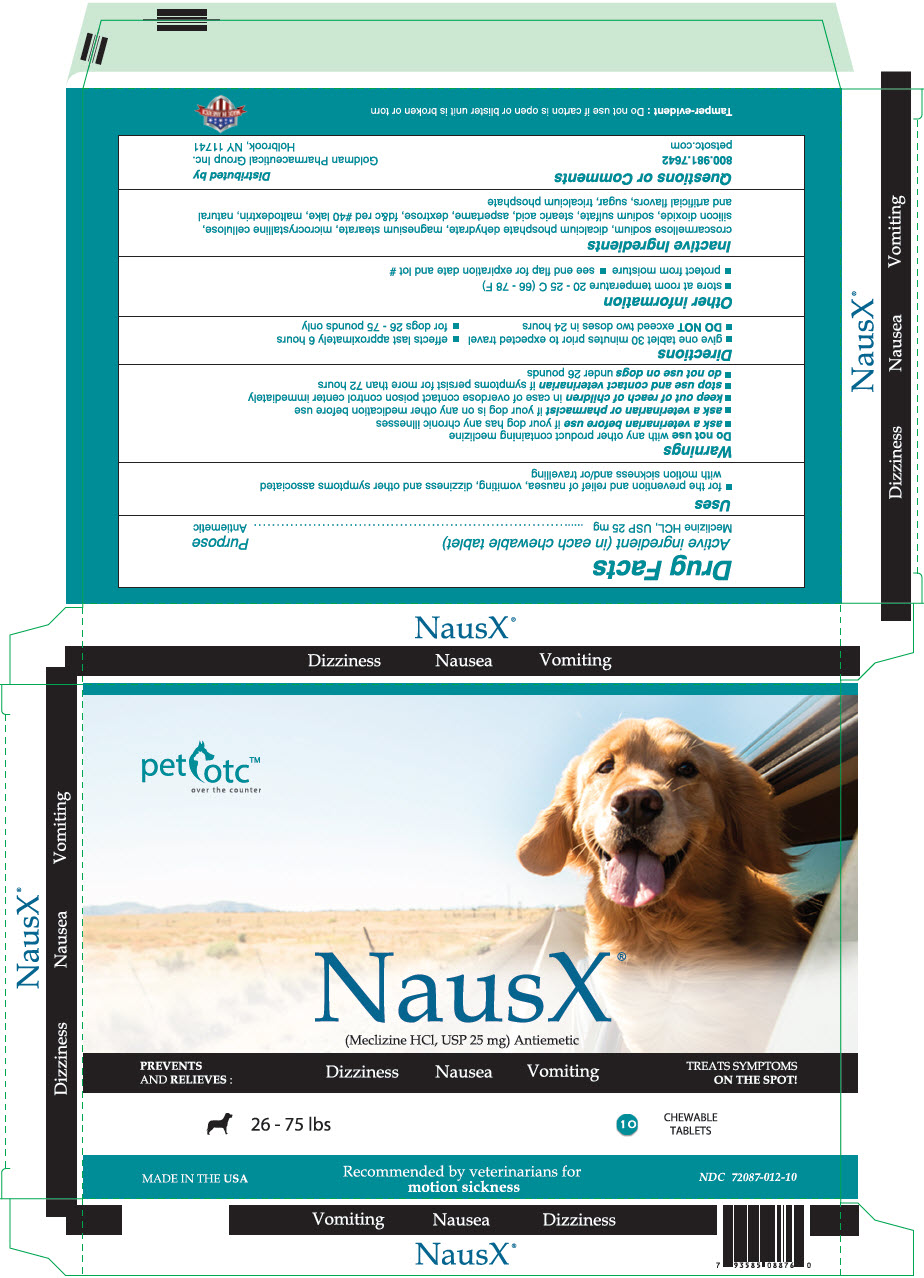 DRUG LABEL: NausX
NDC: 72087-012 | Form: TABLET, CHEWABLE
Manufacturer: Goldman Pharmaceutical Group Inc
Category: animal | Type: OTC ANIMAL DRUG LABEL
Date: 20190219

ACTIVE INGREDIENTS: MECLIZINE HYDROCHLORIDE 25 mg/1 1
INACTIVE INGREDIENTS: ASPARTAME; CROSCARMELLOSE SODIUM; DEXTROSE, UNSPECIFIED FORM; MAGNESIUM STEARATE; MALTODEXTRIN; MICROCRYSTALLINE CELLULOSE; SILICON DIOXIDE; SODIUM SULFATE; SUCROSE; TRICALCIUM PHOSPHATE

NausX®

Drug Facts

Active ingredient (in each chewable tablet) | Purpose
Meclizine HCL, USP 25 mg | Antiemetic

Uses

- for the prevention and relief of nausea, vomiting, dizziness and other symptoms associated with motion sickness and/or travelling

Warnings

Do not use with any other product containing meclizine

- ask a veterinarian before use if your dog has any chronic illnesses
- ask a veterinarian or pharmacist if your dog is on any other medication before use
- keep out of reach of children in case of overdose contact poison control center immediately
- stop use and contact veterinarian if symptoms persist for more than 72 hours
- do not use on dogs under 26 pounds

Directions

- give one tablet 30 minutes prior to expected travel
- effects last approximately 6 hours
- DO NOT exceed two doses in 24 hours
- for dogs 26 - 75 pounds only

Other information

- store at room temperature 20 - 25 C (66 - 78 F)
- protect from moisture
- see end flap for expiration date and lot #

Inactive Ingredients

croscarmellose sodium, dicalcium phosphate dehydrate, magnesium stearate, microcrystalline cellulose, silicon dioxide, sodium sulfate, stearic acid, aspertame, dextrose, fd&c red #40 lake, maltodextrin, natural and artificial flavors, sugar, tricalcium phosphate

Questions or Comments

800.981.7642
petsotc.com

Distributed by
Goldman Pharmaceutical Group Inc.
Holbrook, NY 11741

Tamper-evident : Do not use if carton is open or blister unit is broken or torn

MADE IN AMERICA

PRINCIPAL DISPLAY PANEL - 25 mg Tablet Blister Pack Carton

pet otc™
over the counter

NausX®
(Meclizine HCl, USP 25 mg) Antiemetic

PREVENTS
AND RELIEVES:
Dizziness
Nausea
Vomiting
TREATS SYMPTOMS
ON THE SPOT!

26 - 75 lbs
10
CHEWABLE
TABLETS

MADE IN THE USA

Recommended by veterinarians for
motion sickness

NDC 72087-012-10